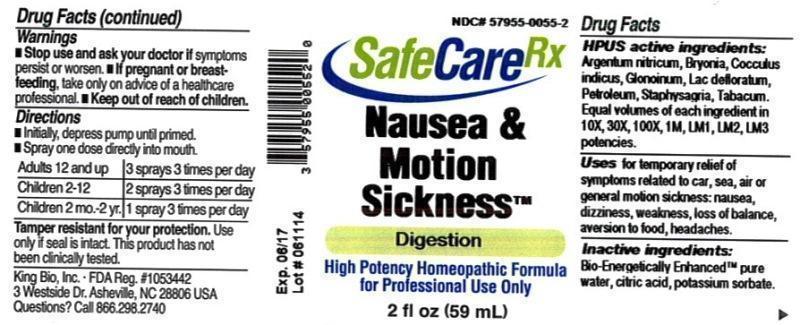 DRUG LABEL: Nausea and Motion Sickness
NDC: 57955-0055 | Form: LIQUID
Manufacturer: King Bio Inc.
Category: homeopathic | Type: HUMAN OTC DRUG LABEL
Date: 20140929

ACTIVE INGREDIENTS: SILVER NITRATE 10 [hp_X]/59 mL; BRYONIA ALBA ROOT 10 [hp_X]/59 mL; ANAMIRTA COCCULUS SEED 10 [hp_X]/59 mL; NITROGLYCERIN 10 [hp_X]/59 mL; SKIM MILK 10 [hp_X]/59 mL; KEROSENE 10 [hp_X]/59 mL; DELPHINIUM STAPHISAGRIA SEED 10 [hp_X]/59 mL; TOBACCO LEAF 10 [hp_X]/59 mL
INACTIVE INGREDIENTS: WATER; CITRIC ACID MONOHYDRATE; POTASSIUM SORBATE

Nausea and Motion Sickness

Drug Facts

____________________________________________________________________________________________________________________

HPUS active ingredients: Argentum nitricum, Bryonia, Cocculus indicus, Glonoinum, Lac defloratum, Petroleum, Staphysagria, Tabacum. Equal volumes of each ingredient in 10X, 30X, 100X, 1M, LM1, LM2, LM3 potencies.

INDICATIONS AND USAGE

Uses for temporary relief of symptoms related to car, sea, air or general motion sickness: nausea, dizziness, weakness, loss of balance, aversion to food, headaches.

INACTIVE INGREDIENT

Inactive ingredients: Bio-Energetically Enhanced pure water, citric acid, potassium sorbate.

Warnings

- Stop use and ask your doctor if symptoms persist or worsen.
- If pregnant or breast-feeding, take only on advice of a healthcare professional.

- Keep out of reach of children.

Directions:

- Initially, depress pump until primed.
- Spray one dose directly into mouth.
- Adults 12 and up: 3 sprays 3 times per day.
- Children 2-12: 2 sprays 3 times per day.
- Children 2 mo-2 yr: 1 spray 3 times per day.

OTHER SAFETY INFORMATION

Tamper resistant for your protection. Use only if safety seal is intact. This product has not been clinically tested.

PURPOSE

Uses for temporary relief of symptoms related to car, sea, air or general motion sickness:

- nausea
- dizziness
- weakness
- loss of balance
- aversion to food
- headaches